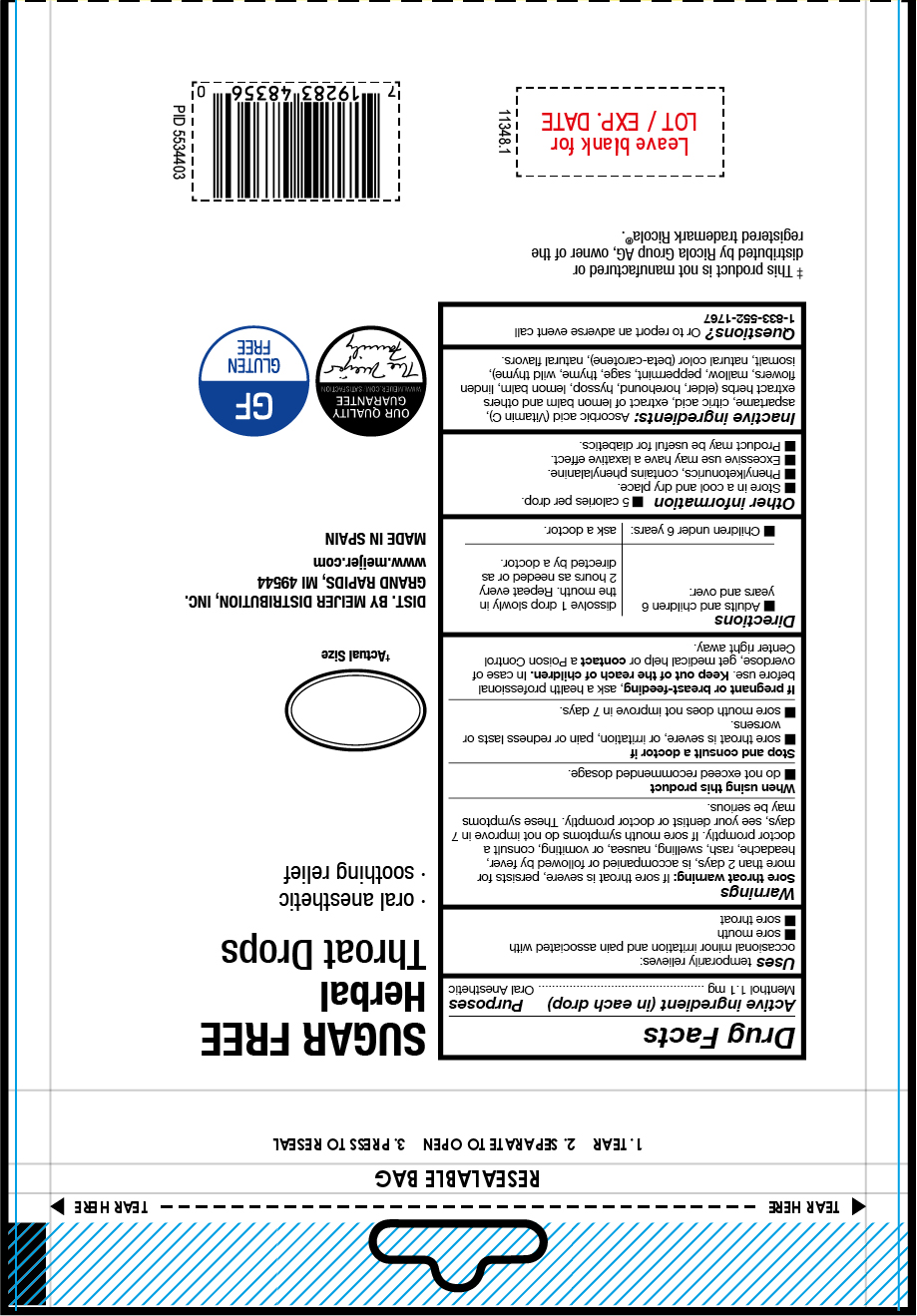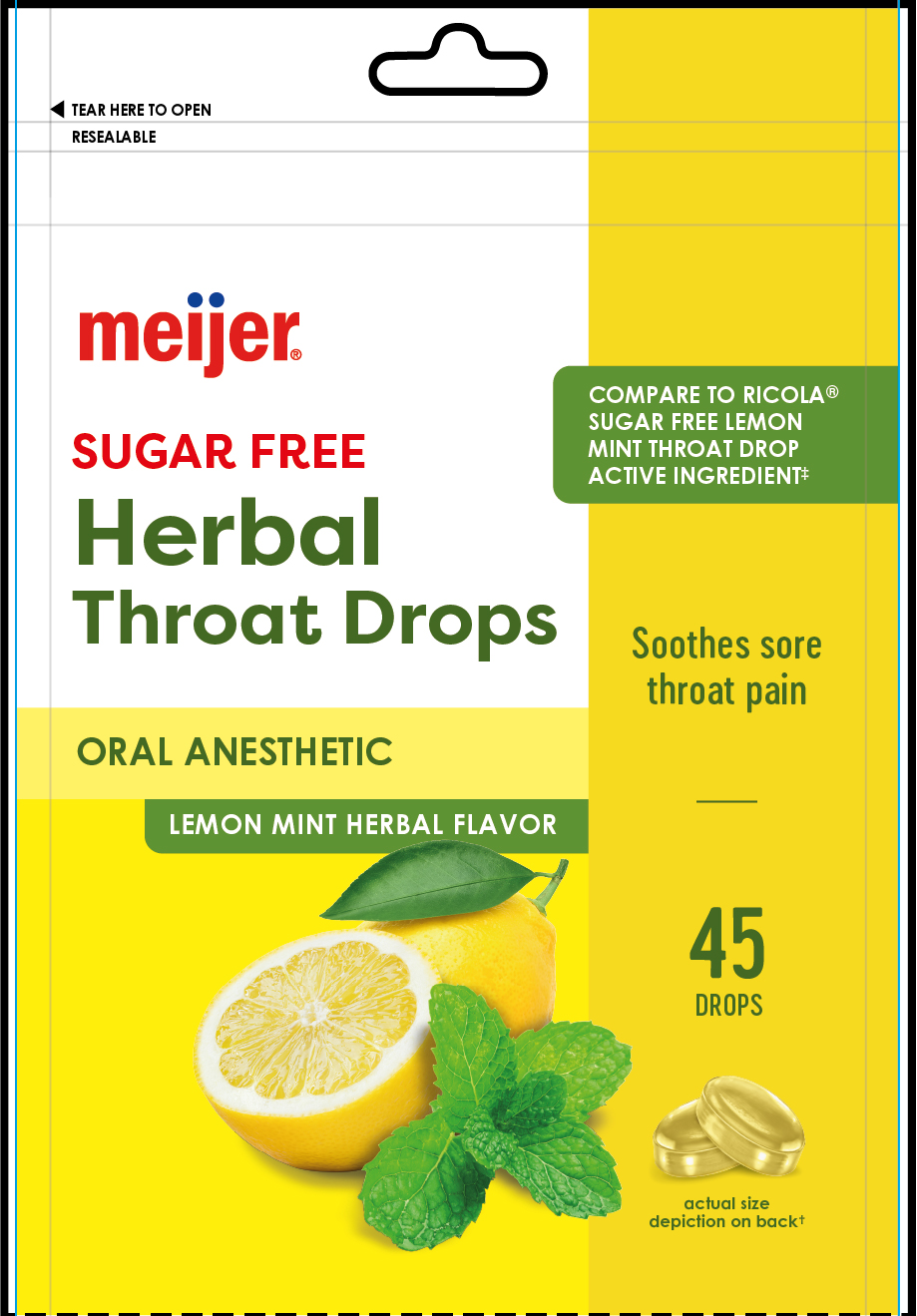 DRUG LABEL: Herbal Throat Drops
NDC: 79481-0024 | Form: PASTILLE
Manufacturer: Meijer, Inc.
Category: otc | Type: HUMAN OTC DRUG LABEL
Date: 20250616

ACTIVE INGREDIENTS: MENTHOL 1.1 mg/1 1
INACTIVE INGREDIENTS: FLAVONE; SAGE; WILD THYME; MALVA SYLVESTRIS (MALLOW) LEAF POWDER; ASCORBIC ACID; ASPARTAME; CITRIC ACID MONOHYDRATE; LEMON BALM OIL; HOREHOUND; HYSSOP OIL; LINDEN LEAF; SAMBUCUS NIGRA FLOWER; PEPPERMINT; BETA CAROTENE; ISOMALT; THYME

Herbal Throat Drops
Lemon Mint

Active ingredient

- Menthol 1.1 mg

PURPOSE

Uses temporarily relieves:

ocassional minor irritation and pain associated with

- sore mouth
- sore throat

INDICATIONS AND USAGE

Uses temporarily relieves:
ocassional minor irritation and pain associated with

- sore mouth
- sore throat

Warnings

Sore throat warning: If sore throat is severe, persists for more than 2 days, is accompanied or followed by fever, headache, rash, swelling, nausea, or vomiting, consult a doctor promptly. If sore mouth symptoms do not improve in 7 days, see your dentist or doctor promptly. These symptoms may be serious

Stop and consult a doctor if

- sore throat is severe, or irritation, pain or redness last or worsens.
- sore mouth does not improve in 7 days.

Stop and consult a doctor if

- sore throat is severe, or irritation, pain or redness last or worsens.
- sore mouth does not improve in 7 days.

PREGNANCY OR BREAST FEEDING

If pregnant or breast-feeding, ask a health professional before use.

Keep out of the reach of children.

OVERDOSAGE

In case of overdose, get medical help or contact a Poison Control Center right away.

Directions

- Adults and children 6 years and over: dissolve 1 drop slowly in mouth. Repeated every 2 hours as needed or as directed by a doctor.
- Children under 6 years: as a doctor

OTHER SAFETY INFORMATION

- Store in a cool and dry place

INACTIVE INGREDIENT

ascorbic acid (Vitamin C), aspartame, citric acid, extract of lemon balm and others extract herbs (elder, horehound, hyssop, lemon balm,linden flowers, mallow, peppermint, sage, thyme, wild thyme), isomalt, natural color (beta-carotene), natural flavors.

QUESTIONS

Questions? or to report and adverse event call: 1-833-552-1767

RECENT MAJOR CHANGES

- Indications and Usage
- Dosage and Administration
- Contraindications
- Warnings and Precautions
- Inactive ingredients